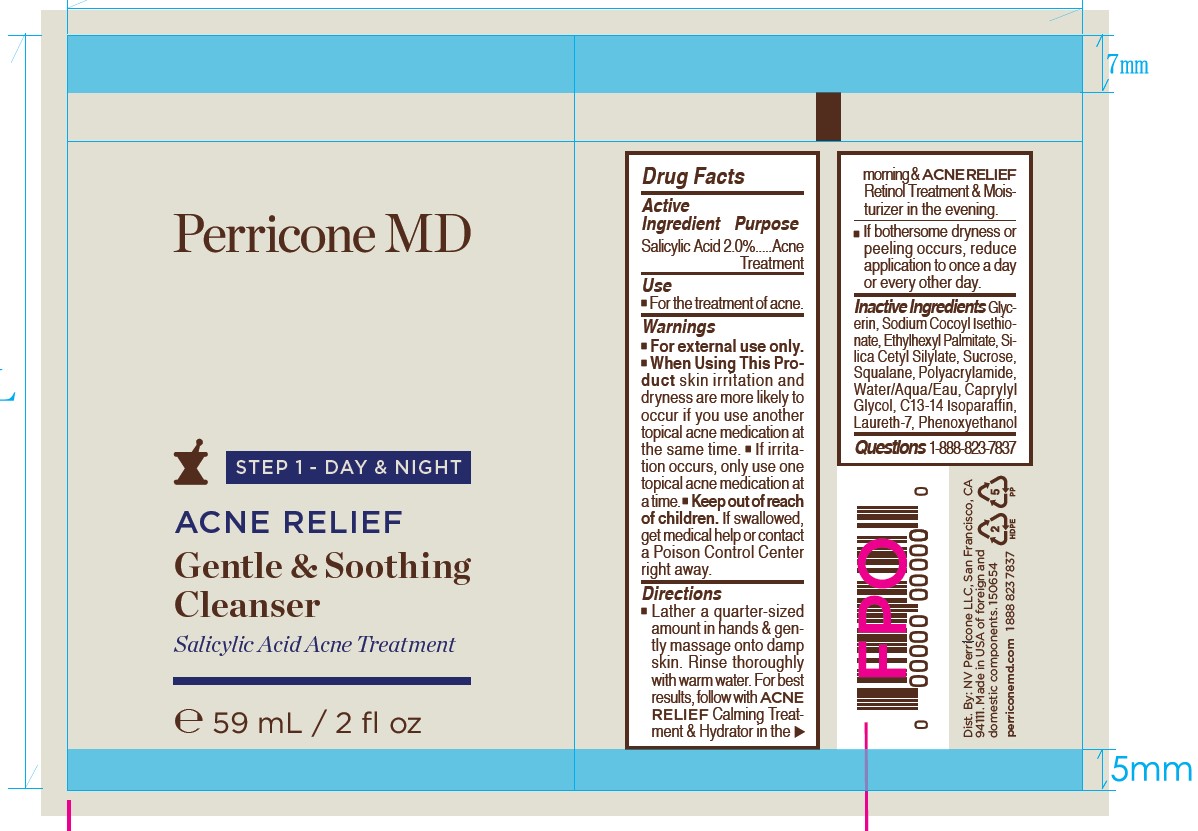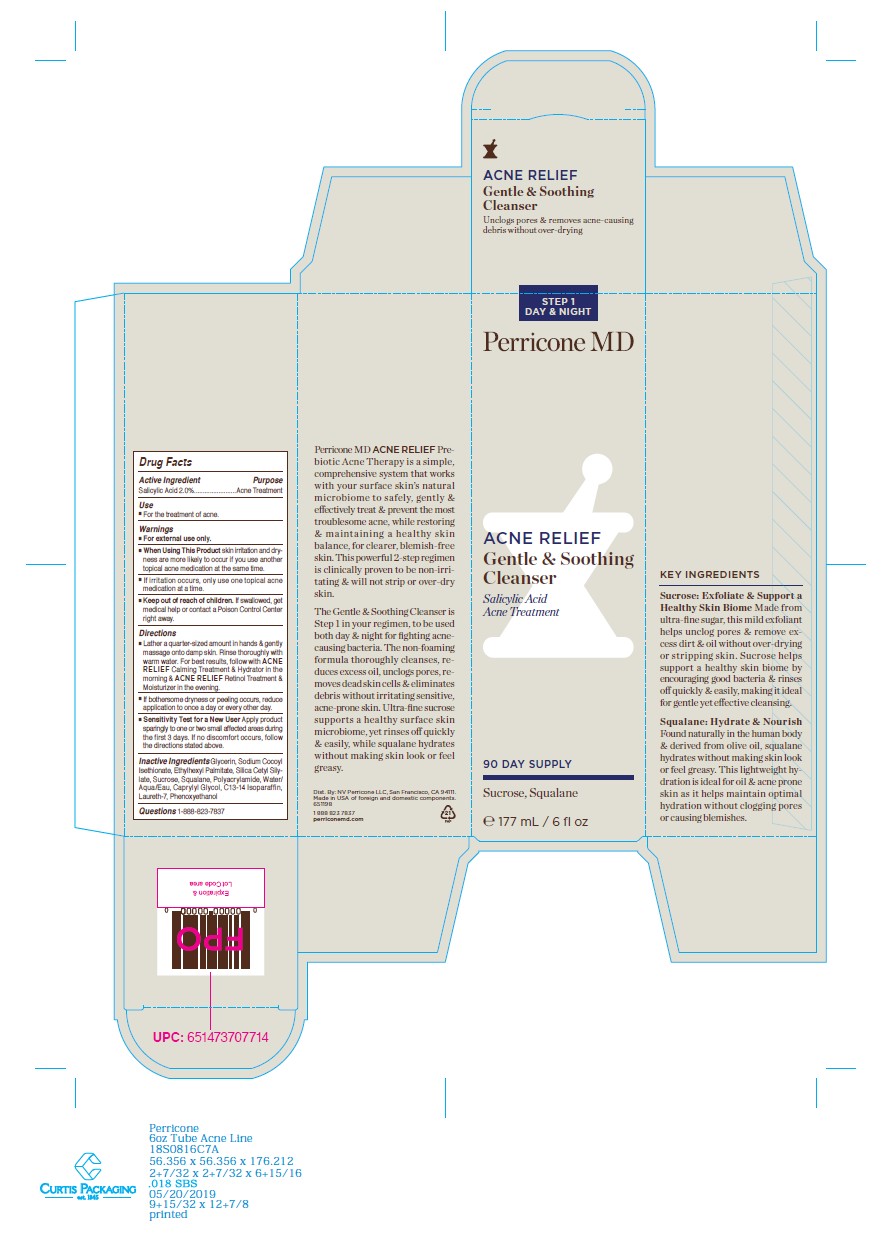 DRUG LABEL: Perricone MD Acne Relief Gentle and Soothing Cleanser
NDC: 84448-539 | Form: GEL
Manufacturer: THG Beauty USA LLC
Category: otc | Type: HUMAN OTC DRUG LABEL
Date: 20251031

ACTIVE INGREDIENTS: SALICYLIC ACID 2 g/100 mL
INACTIVE INGREDIENTS: ETHYLHEXYL PALMITATE; SILICA DIMETHYL SILYLATE; PHENOXYETHANOL; SQUALANE; CAPRYLYL GLYCOL; POLYACRYLAMIDE (10000 MW); WATER; SUCROSE; C13-14 ISOPARAFFIN; GLYCERIN; SODIUM COCOYL ISETHIONATE; LAURETH-7

ACTIVE INGREDIENT

- Salicylic Acid 2.0%

PURPOSE

- Acne Treatment

INDICATIONS AND USAGE

- For the treatment of acne.

WARNINGS

- For external use only.

WHEN USING

- skin irritation and dryness are more likely to occur if you use another topical acne medication at the same time. If irritation occurs, only use one tropical acne medication at a time.

KEEP OUT OF REACH OF CHILDREN

- If swallowed, get medical help or contact a Poison Control Center right away.

DOSAGE AND ADMINISTRATION

- Lather a quarter-sized amount in hands & gently massage onto damp skin. Rinse throughly with warm water. For best results, follow with ACNE RELIEF Calming Treatment & Hydrator in the morning & ACNE RELIEF Retinol Treatment & Moisturizer in the evening.
- If bothersome dryness or peeling occurs, reduce application to once a day or every other day.
- Sensitivity Test for a New User Apply product sparingly to one or two small affected areas during the first 3 days. if no discomfort occurs, follow the directions stated above.

INACTIVE INGREDIENT

Glycerin, Sodium Cocoyl Isethionate, Ethylhexyl Palmitate, Silica Cetyl Silylate, Sucrose, Phenoxyethanol, Polyacrylamide, Water/Aqua/Eau, Caprylyl Glycol, C13-14 Isoparaffin, Squalane, Laureth-7

QUESTIONS

- 1-888-823-7837